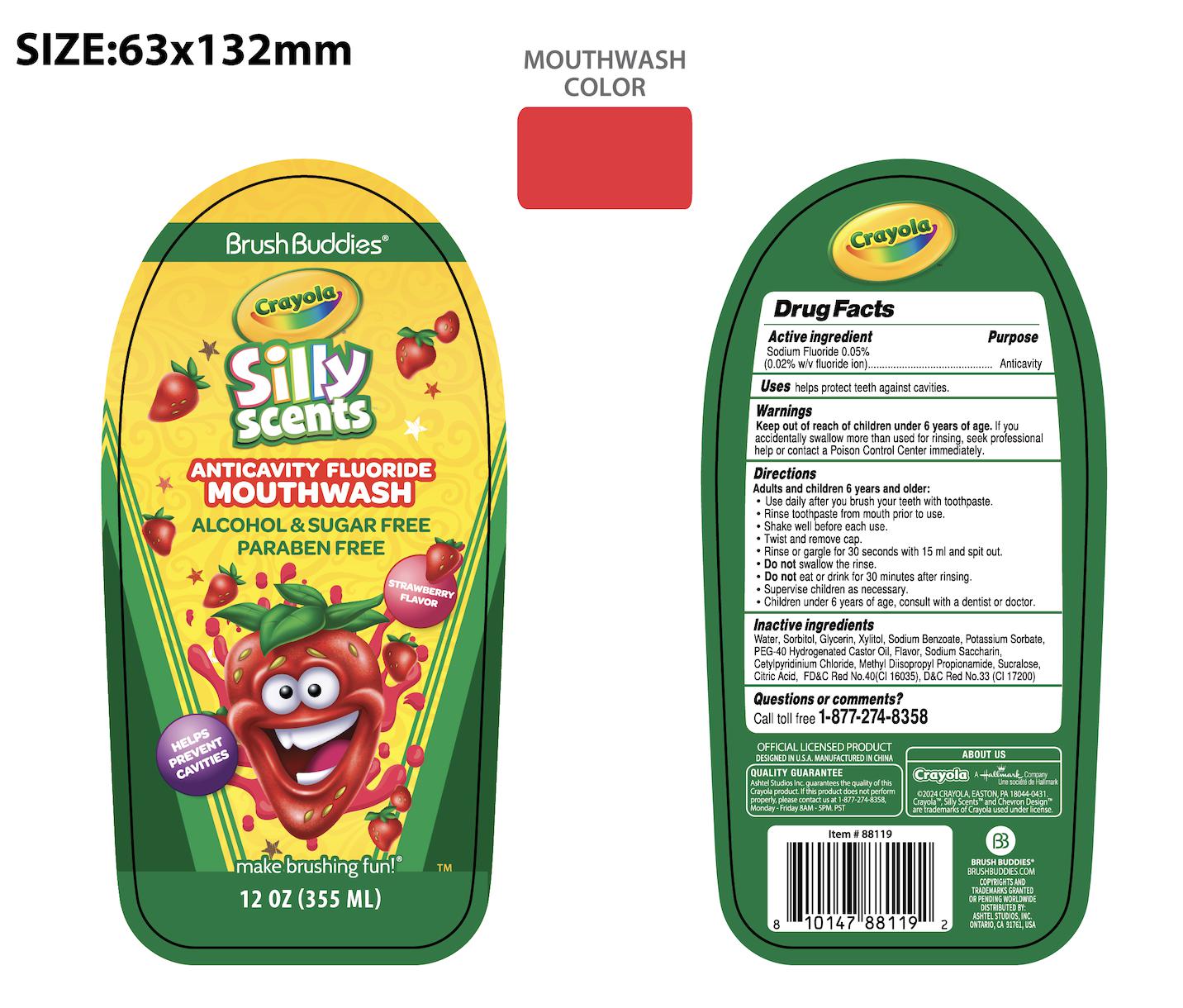 DRUG LABEL: BRUSH BUDDIES CRAYOLA ANTICAVITY FLUORIDE STRAWBERRY
NDC: 73928-046 | Form: LIQUID
Manufacturer: Kingkey MBC Life Technology Group Co.,Ltd
Category: otc | Type: HUMAN OTC DRUG LABEL
Date: 20251211

ACTIVE INGREDIENTS: SODIUM FLUORIDE 0.05 g/100 mL
INACTIVE INGREDIENTS: POLYOXYL 40 HYDROGENATED CASTOR OIL; CITRIC ACID MONOHYDRATE; D&C RED NO. 33; POTASSIUM SORBATE; METHYL DIISOPROPYL PROPIONAMIDE; WATER; GLYCERIN; SUCRALOSE; XYLITOL; SODIUM BENZOATE; SORBITOL; SACCHARIN SODIUM; CETYLPYRIDINIUM CHLORIDE; FD&C RED NO. 40

BRUSH BUDDIES CRAYOLA ANTICAVITY FLUORIDE STRAWBERRY-73928-033 (0.05%)

Active ingredient

SODIUM FLUORIDE 0.05%

Purpose

(0.02% w/v fluoride ion)---------Anticavity

Uses

helps protect teeth against cavities

Warnings

Keep out of reach of children under 6 years of age.lf you accidentally swallow more than used for rinsing, seek
professional help or contact a Poison Control Center immediately.

Directions

Adults and children 6 years and older:

- Use daily after you brush your teeth with toothpaste
- Rinse toothpaste from mouth prior to use.
- Shake well before each use.Twist and remove cap.
- Rinse or gargle for 30 seconds with 15 ml and spit out.
- Do Not sllo the ins.
- Do Not eat or drink for 30 minutes after rinsing
- Supervise children as necessary.
- Children under 6 years of age：consult with a dentist or doctor.

Questions or comments?

Call toll free 1-877-274-8358